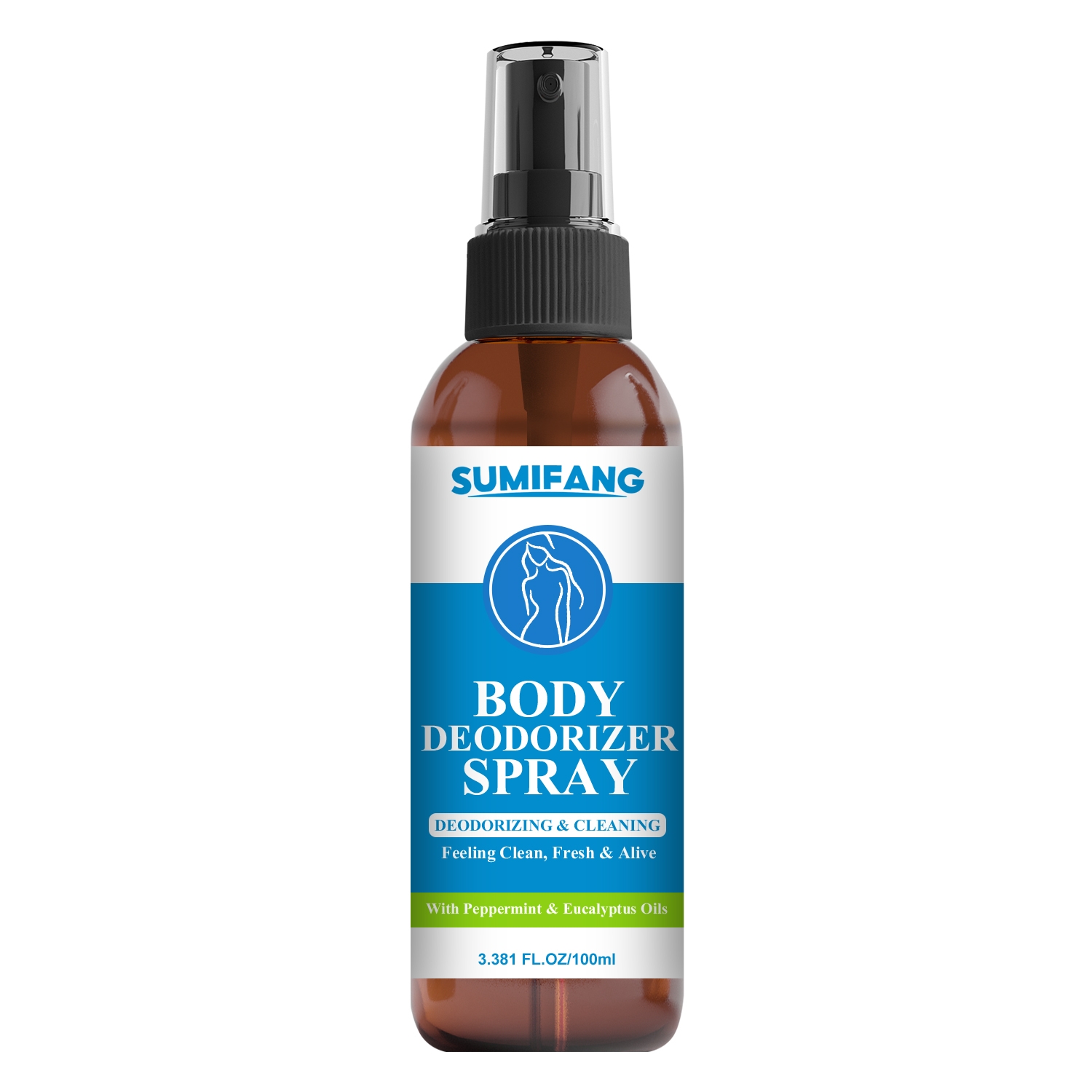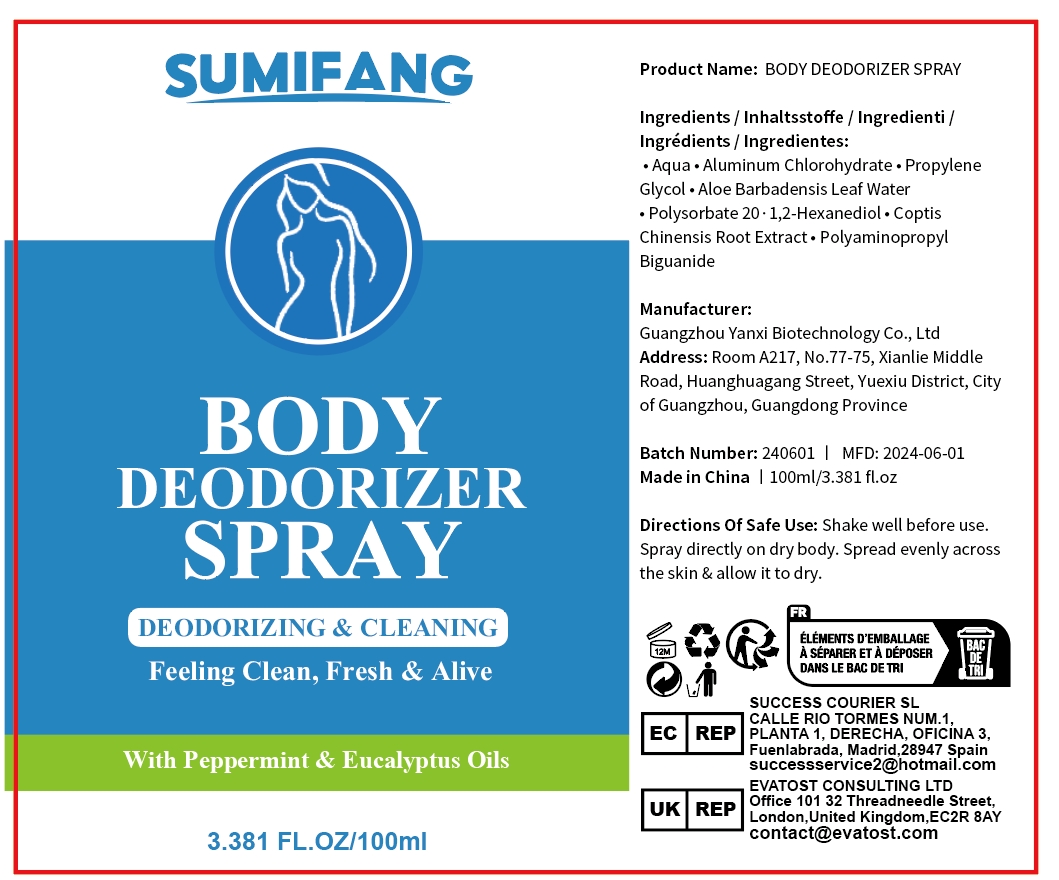 DRUG LABEL: BODY DEODORIZERSPRAY
NDC: 84025-106 | Form: SPRAY
Manufacturer: Guangzhou Yanxi Biotechnology Co.. Ltd
Category: otc | Type: HUMAN OTC DRUG LABEL
Date: 20240801

ACTIVE INGREDIENTS: ALUMINUM CHLOROHYDRATE ANHYDROUS 5 mg/100 mL; POLYSORBATE 20 3 mg/100 mL
INACTIVE INGREDIENTS: WATER

DOSAGE AND ADMINISTRATION

Spray for eliminating body odor

WARNINGS

keep out of children

INACTIVE INGREDIENT

Aqua

INDICATIONS AND USAGE

For eliminating body odor

Keep out of children

PURPOSE

Eliminates body odor and moisturizes skin